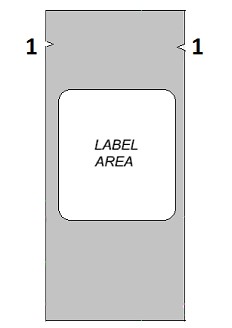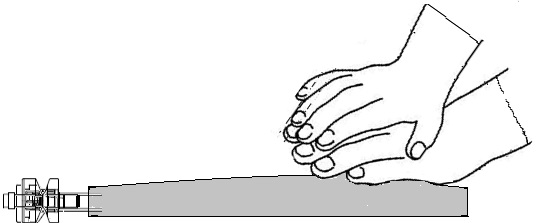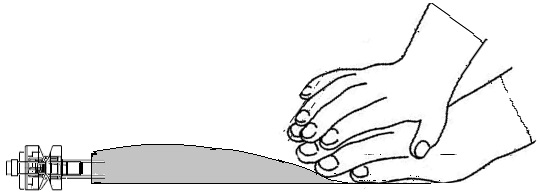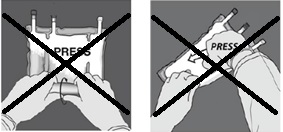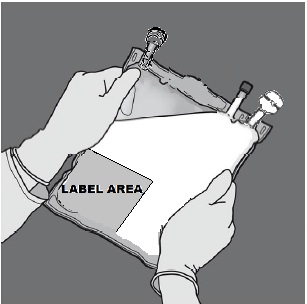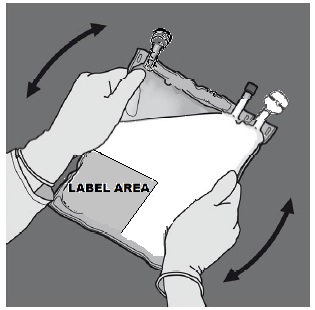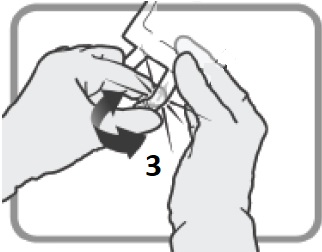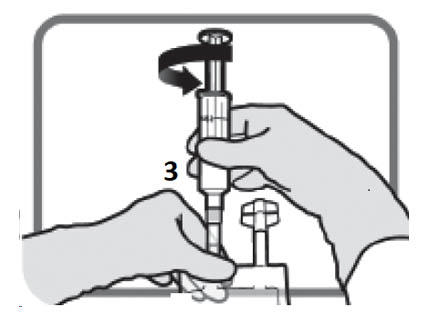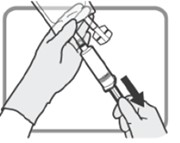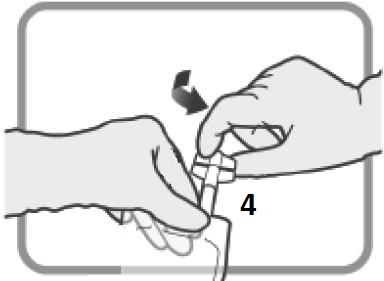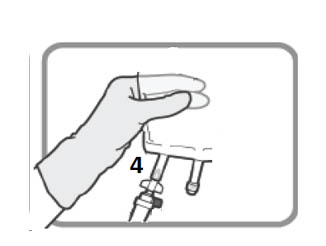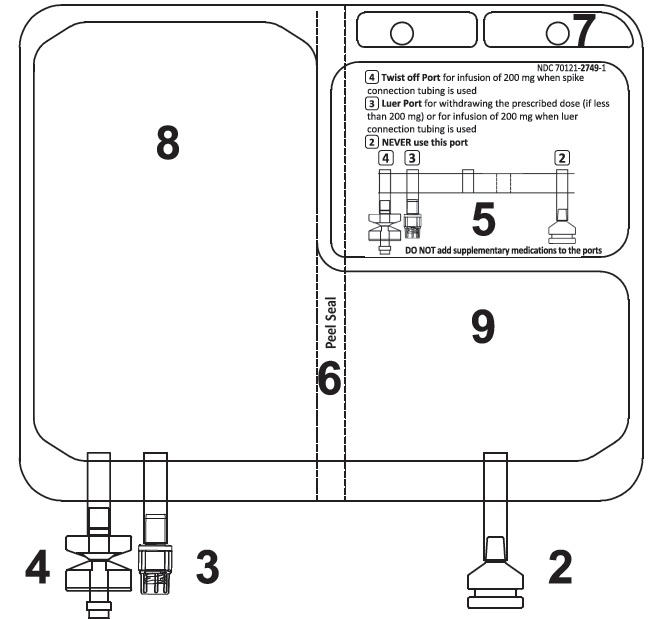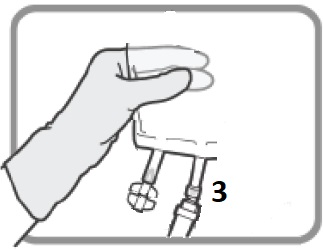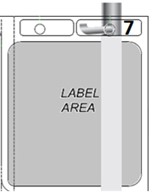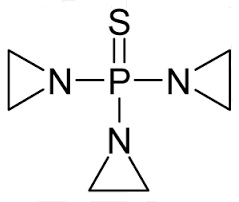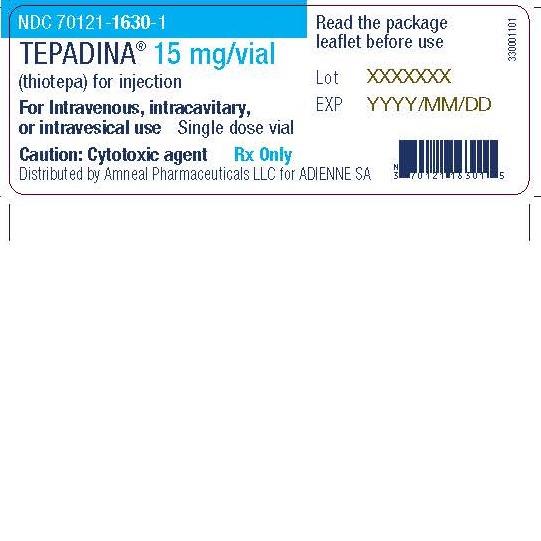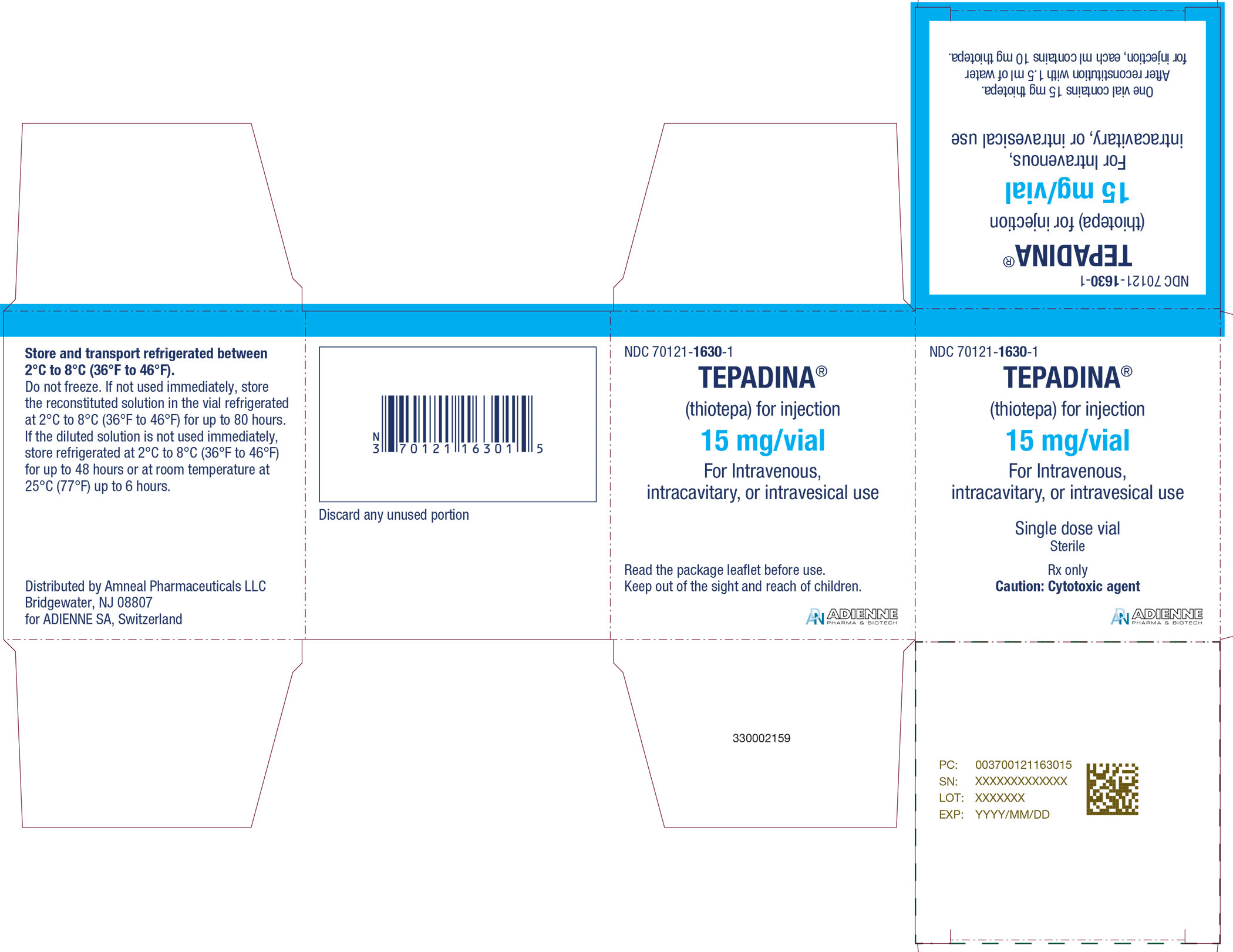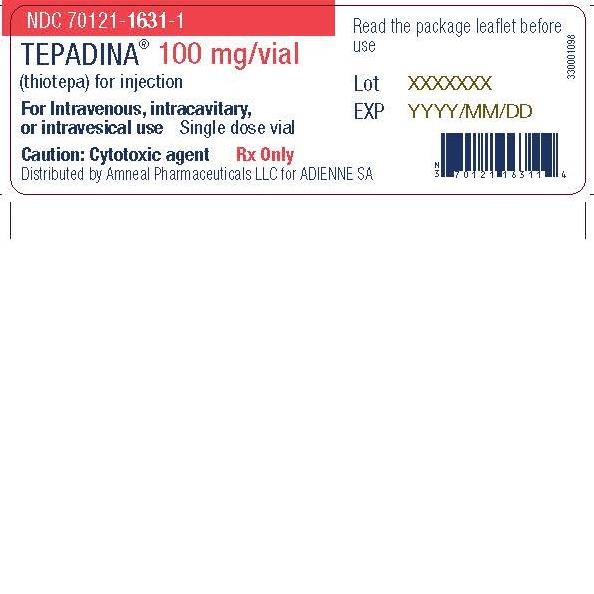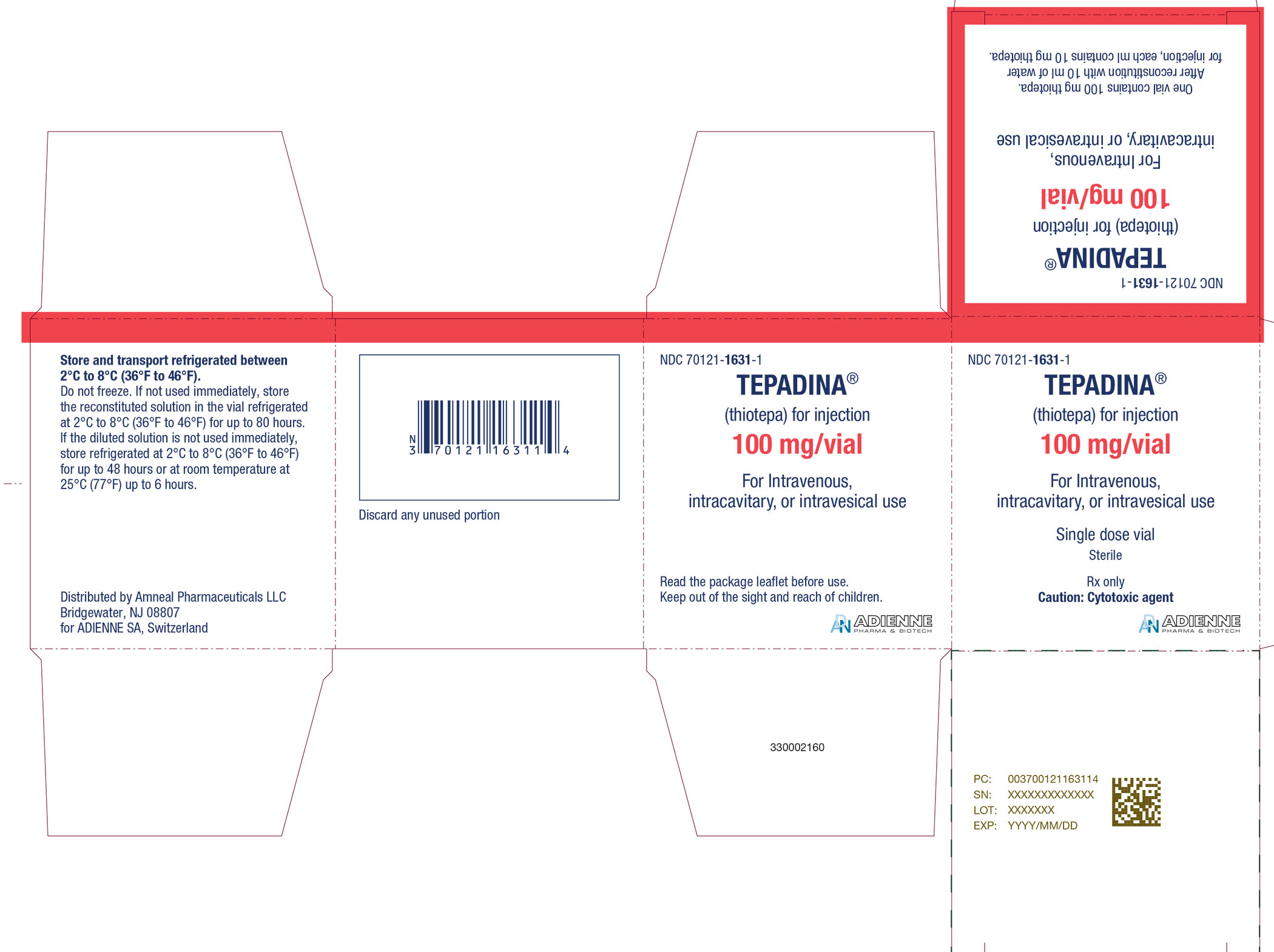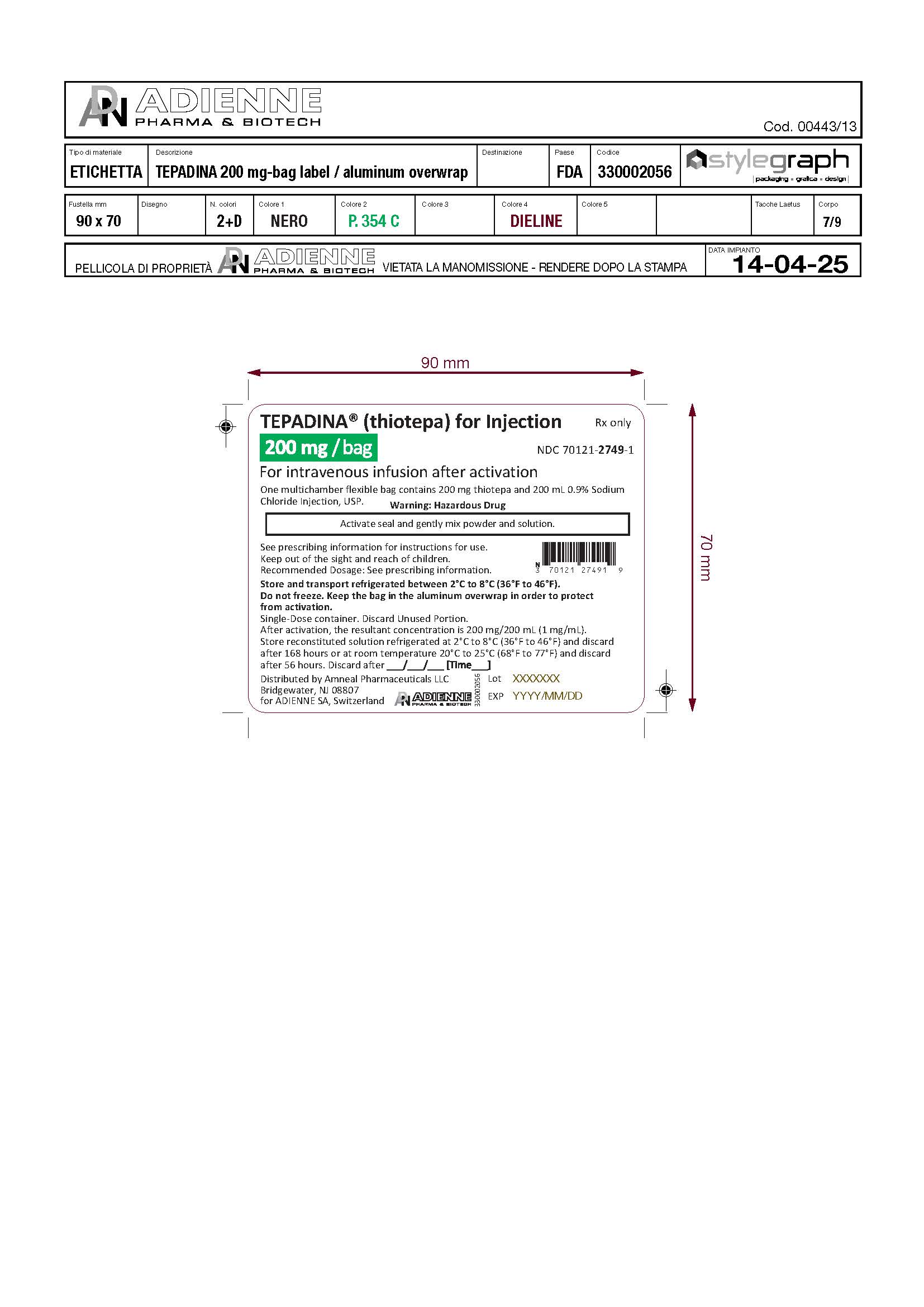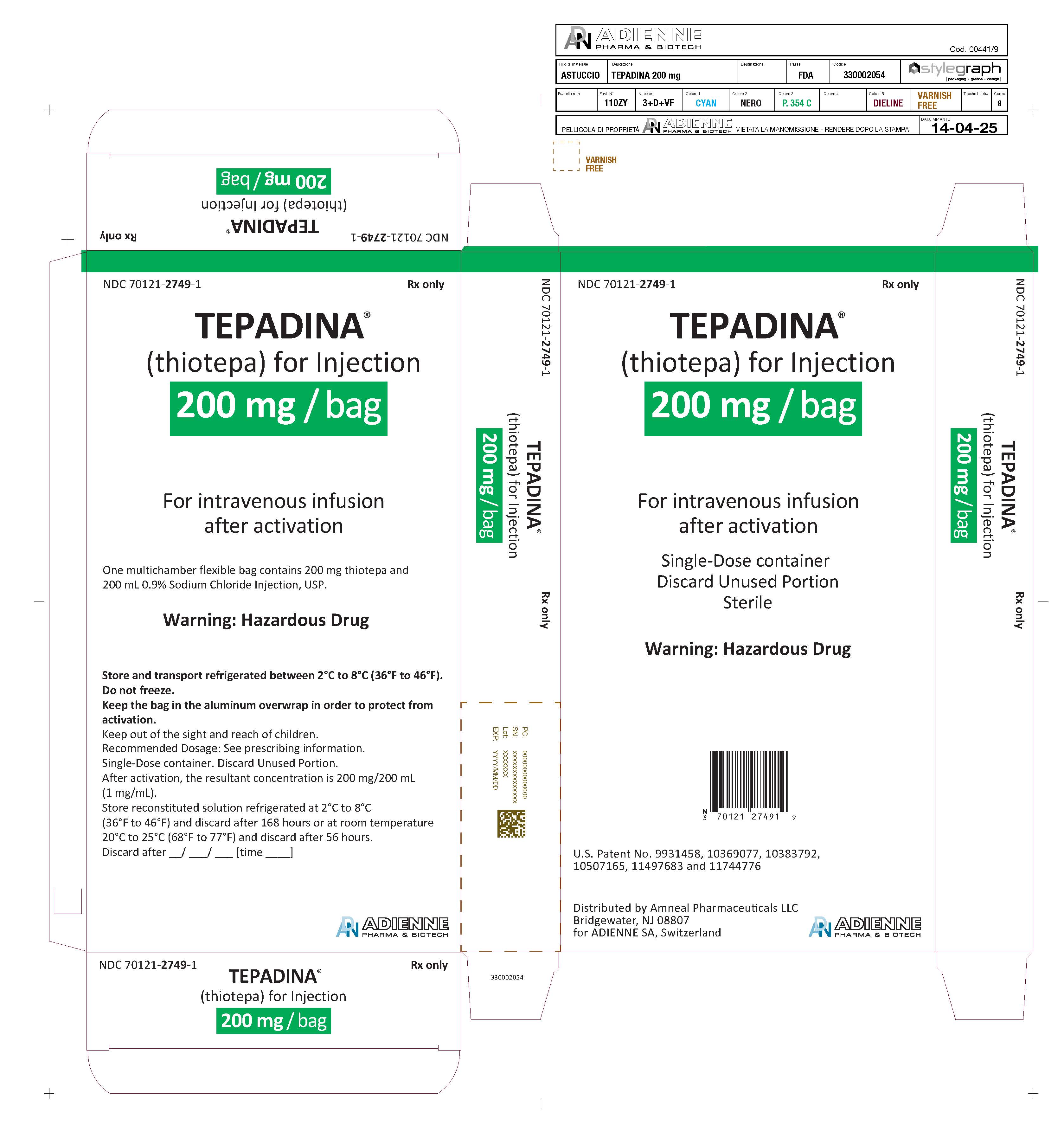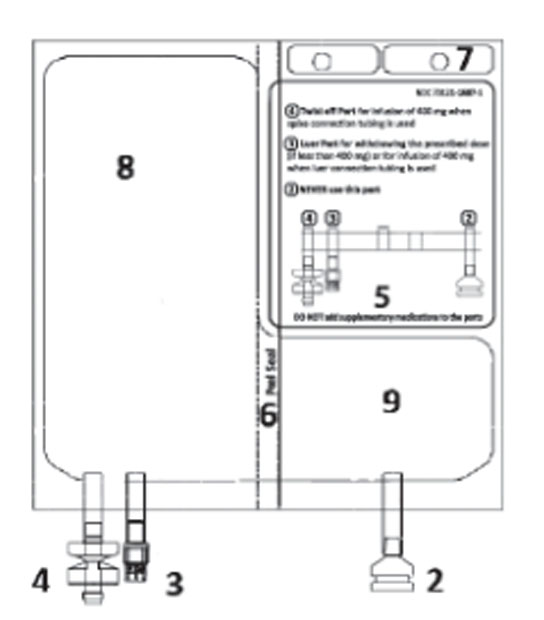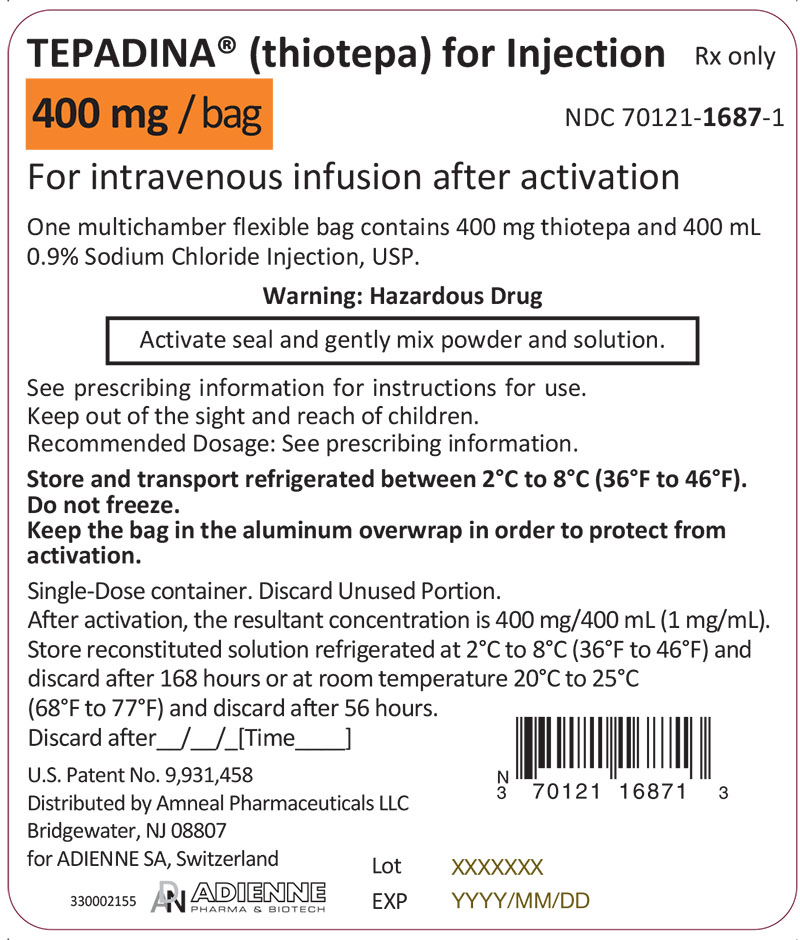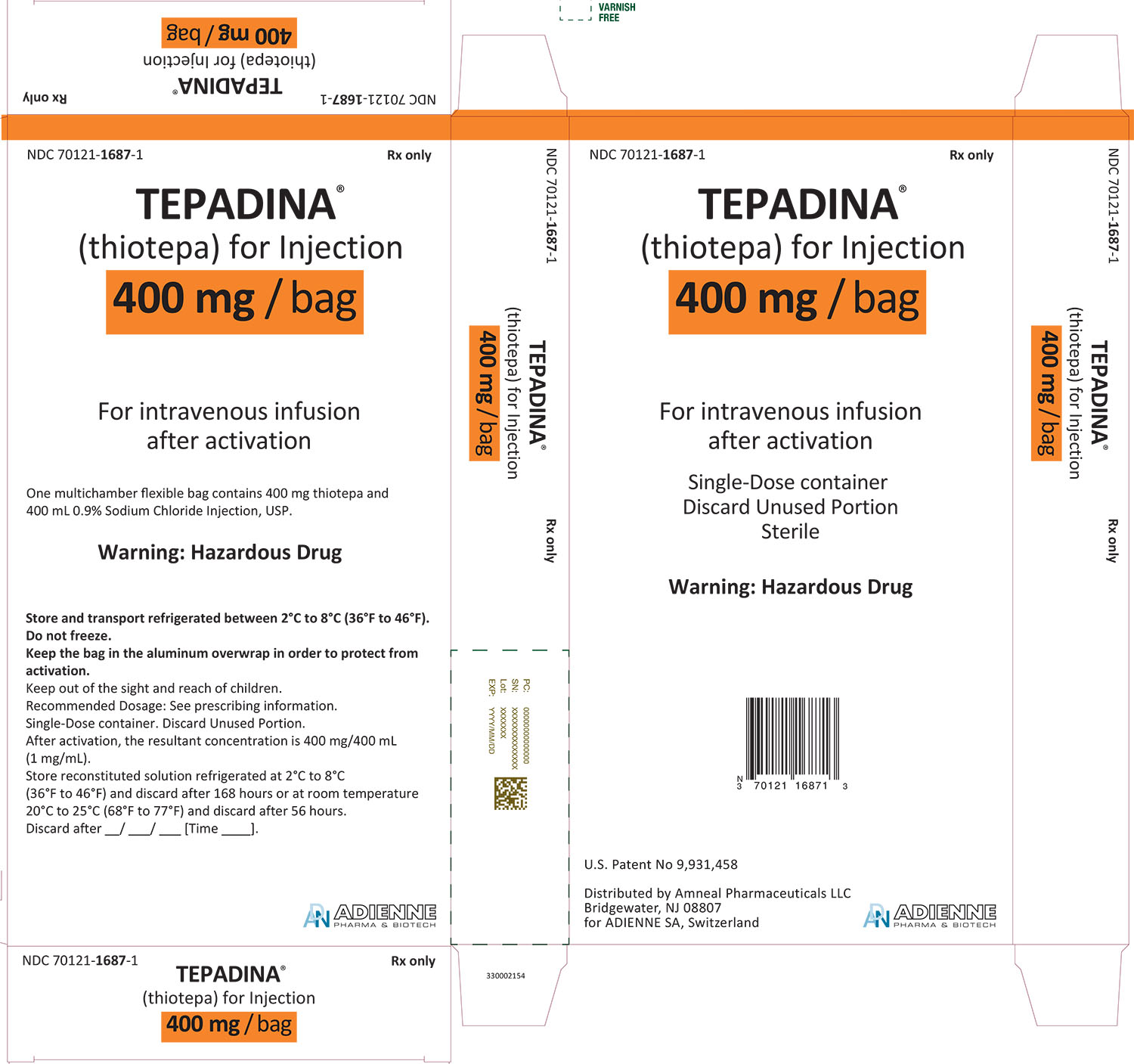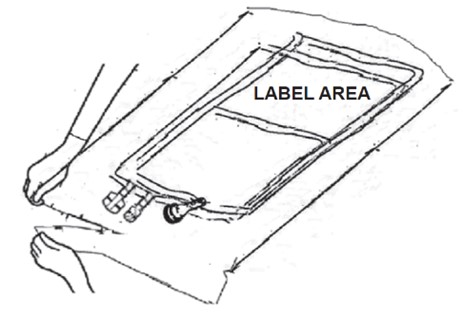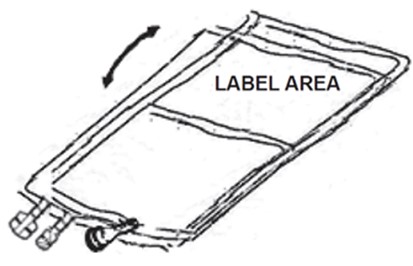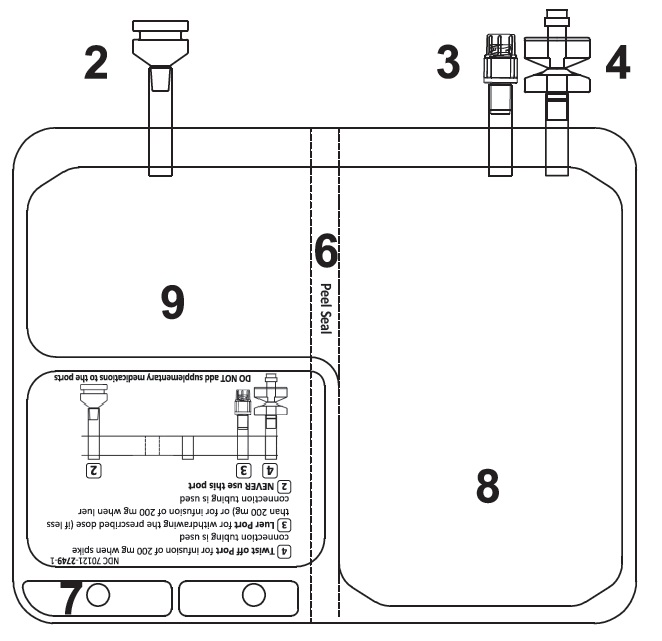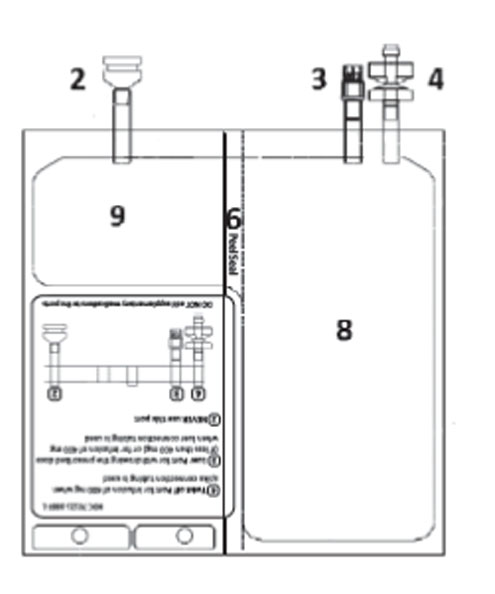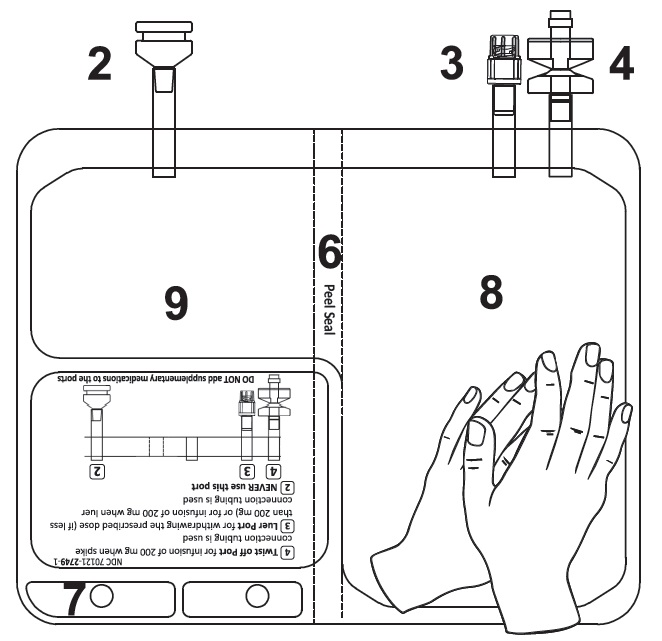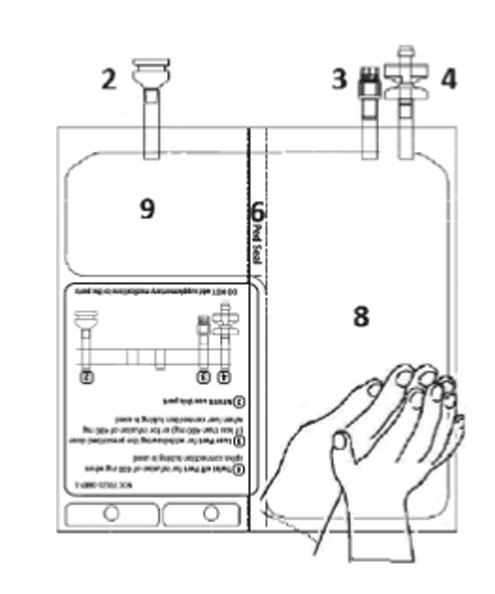 DRUG LABEL: TEPADINA
NDC: 70121-1630 | Form: INJECTION, POWDER, FOR SOLUTION
Manufacturer: Amneal Pharmaceuticals LLC
Category: prescription | Type: HUMAN PRESCRIPTION DRUG LABEL
Date: 20260130

ACTIVE INGREDIENTS: THIOTEPA 15 mg/1 1

HIGHLIGHTS OF PRESCRIBING INFORMATION

These highlights do not include all the information needed to use TEPADINA® safely and effectively. See full prescribing information for TEPADINA®.
TEPADINA® (thiotepa) for injection, for intravenous, intracavitary, or intravesical use.
Initial U.S. Approval: 1959

WARNING: SEVERE MYELOSUPPRESSION and CARCINOGENICITY

See full prescribing information for complete boxed warning.

- May cause severe marrow suppression or ablation with resulting infection or bleeding. Monitor hematologic laboratory parameters. (5.1)
- Potentially carcinogenic in humans. (5.7)

RECENT MAJOR CHANGES

Dosage and Administration, Preparation Instructions (2.2) 4/2025

Dosage and Administration, Instruction for Use of the Multichamber Flexible Bag (2.3) 4/2025

1 INDICATIONS AND USAGE

TEPADINA (thiotepa) is an alkylating drug indicated:

- To reduce the risk of graft rejection when used in conjunction with high-dose busulfan and cyclophosphamide as a preparative regimen for allogeneic hematopoietic progenitor (stem) cell transplantation (HSCT) for pediatric patients with class 3 beta-thalassemia. (1.1, 14)
- For treatment of adenocarcinoma of the breast or ovary. (1.2)
- For controlling intracavitary effusions secondary to diffuse or localized neoplastic diseases of various serosal cavities. (1.3)
- For treatment of superficial papillary carcinoma of the urinary bladder. (1.4)

2 DOSAGE AND ADMINISTRATION

- The recommended dosage of TEPADINA for class 3 beta-thalassemia is two administrations of 5 mg/kg given by intravenous infusion approximately 12 hours apart on Day -6 before allogeneic HSCT in conjunction with high-dose busulfan and cyclophosphamide. (2.1)
- The recommended dosage of TEPADINA for treatment of adenocarcinoma of the breast or ovary is 0.3 mg/kg to 0.4 mg/kg by intravenous infusion. (2.1)
- The recommended dosage of TEPADINA for treatment of malignant effusions is 0.6 mg/kg to 0.8 mg/kg intracavitary. (2.1)
- The recommended dosage of TEPADINA for treatment of superficial papillary carcinoma of the urinary bladder is 60 mg in 30 mL to 60 mL of 0.9% Sodium Chloride Injection into the bladder by catheter. (2.1)
- See Full Prescribing Information for preparation and administration instructions. (2.2, 2.3)

3 DOSAGE FORMS AND STRENGTHS

- For injection: 15 mg, lyophilized white powder in single-dose vial for reconstitution. (3)
- For injection: 100 mg, lyophilized white powder in single-dose vial for reconstitution. (3)
- For injection: 200 mg, lyophilized white powder and 200 mL 0.9% Sodium Chloride Injection in single-dose multichamber flexible bag for reconstitution. (3)
- For injection: 400 mg, lyophilized white powder and 400 mL 0.9% Sodium Chloride Injection in single-dose multichamber flexible bag for reconstitution. (3)

4 CONTRAINDICATIONS

- Hypersensitivity to the active substance (4).
- Concomitant use with live or attenuated vaccines (4).

5 WARNINGS AND PRECAUTIONS

- Cutaneous toxicity: Cleanse skin at least twice daily through 48 hours after the last dose of TEPADINA. (5.3)
- Embryo-Fetal toxicity: Can cause fetal harm. Advise females of reproductive potential and males with female partners of reproductive potential of the potential risk to a fetus and to use effective contraception. (5.8)

6 ADVERSE REACTIONS

The most common adverse reactions (incidence greater than 10%) are neutropenia, anemia, thrombocytopenia, elevated alanine aminotransferase, elevated aspartate aminotransferase, elevated bilirubin, mucositis, cytomegalovirus infection, hemorrhage, diarrhea, hematuria and rash. (6.1)

To report SUSPECTED ADVERSE REACTIONS, contact ADIENNE at 844-668-3940 or FDA at 1-800-FDA-1088 or www.fda.gov/medwatch.

8 USE IN SPECIFIC POPULATIONS

- Lactation: Advise not to breastfeed. (8.2)
- Moderate or severe renal impairment: Monitor patients more frequently for toxicity. (8.6, 12.3)
- Moderate or severe hepatic impairment: Monitor patients more frequently for toxicity. (8.7, 12.3)

FULL PRESCRIBING INFORMATION

WARNING: SEVERE MYELOSUPPRESSION and CARCINOGENICITY

- TEPADINA may cause severe marrow suppression, and high doses may cause marrow ablation with resulting infection or bleeding. Monitor hematologic laboratory parameters. Hematopoietic progenitor (stem) cell transplantation (HSCT) is required to prevent potentially fatal complications of the prolonged myelosuppression after high doses of TEPADINA [see Warnings and Precautions (5.1)]
- TEPADINA should be considered potentially carcinogenic in humans [see Warnings and Precautions (5.7)]

RECENT MAJOR CHANGES

Dosage and Administration, Preparation Instructions (2.2) 4/2025

Dosage and Administration, Instruction for Use of the Multichamber Flexible Bag (2.3) 4/2025

1 INDICATIONS AND USAGE

1.1 Class 3 Beta-Thalassemia

TEPADINA is indicated to reduce the risk of graft rejection when used in conjunction with high-dose busulfan and cyclophosphamide as a preparative regimen for allogeneic hematopoietic progenitor (stem) cell transplantation (HSCT) for pediatric patients with class 3 beta-thalassemia [see Clinical Studies (14)].

1.2 Adenocarcinoma of the Breast or Ovary

TEPADINA is indicated for treatment of adenocarcinoma of the breast or ovary.

1.3 Malignant Effusions

TEPADINA is indicated for controlling intracavitary effusions secondary to diffuse or localized neoplastic diseases of various serosal cavities.

1.4 Superficial Papillary Carcinoma of the Urinary Bladder

TEPADINA is indicated for treatment of superficial papillary carcinoma of the urinary bladder.

2 DOSAGE AND ADMINISTRATION

2.1 Recommended Dosage

Class 3 Beta-Thalassemia

The recommended dosage of TEPADINA in pediatric patients is two administrations of 5 mg/kg given by intravenous infusion approximately 12 hours apart on Day -6 before allogeneic HSCT in conjunction with high-dose busulfan and cyclophosphamide as outlined in Table 1. See Prescribing Information for cyclophosphamide and busulfan for information on these drugs.

Table 1: Dosage Regimen For Allogeneic HSCT In Pediatric Patients With Class 3 Beta-Thalassemia

Treatment | Day prior to transplantation
 | Day ‑10 | Day ‑9 | Day ‑8 | Day ‑7 | Day ‑6 | Day ‑5 | Day ‑4 | Day ‑3 | Day ‑2 | Day ‑1 | Day 0
Busulfan intravenous weight-based dose * | ▲ | ▲ | ▲ | ▲
TEPADINA intravenous 5 mg/kg twice |  |  |  |  | ▲
Cyclophosphamide intravenous 40 mg/kg/day |  |  |  |  |  | ▲ | ▲ | ▲ | ▲
Stem cell Infusion |  |  |  |  |  |  |  |  |  |  | ▲

*Busulfan intravenous weight-based dose: 1 mg/kg every 6 hours for patients less than 9 kg; 1.2 mg/kg every 6 hours for patients 9 kg to 16 kg; 1.1 mg/kg every 6 hours for patients 16.1 kg to 23 kg; 0.95 mg/kg every 6 hours for patients 23.1 kg to 34 kg; 0.8 mg/kg every 6 hours for patients more than 34 kg.

Infuse TEPADINA via a central venous catheter over 3 hours using an infusion set equipped with a 0.2 micron in-line filter. Prior to and following each infusion, flush the catheter with approximately 5 mL of 0.9% Sodium Chloride Injection.

TEPADINA is excreted through the skin of patients receiving high-dose therapy. Take precautions to prevent skin toxicity [see Warnings and Precautions (5.3)].

Adenocarcinoma of the Breast or Ovary

The recommended dosage of TEPADINA for treatment of adenocarcinoma of the breast or ovary is 0.3 mg/kg to 0.4 mg/kg by intravenous infusion. Doses should be given at 1 to 4 week intervals. Initially the higher dose in the given range is commonly administered. The maintenance dose should be adjusted weekly on the basis of pre-treatment control blood counts and subsequent blood counts. Maintenance dosages should not be administered more frequently than weekly.

Malignant Effusions

The recommended dosage of TEPADINA for treatment of malignant effusions is 0.6 mg/kg to 0.8 mg/kg intracavitary. Administration is usually effected through the same tubing which is used to remove the fluid from the cavity involved. Doses should be given at 1 to 4 week intervals. Initially the higher dose in the given range is commonly administered. The maintenance dose should be adjusted weekly on the basis of pre-treatment control blood counts and subsequent blood counts. Maintenance dosages should not be administered more frequently than weekly.

Superficial Papillary Carcinoma of the Urinary Bladder

The recommended dosage of TEPADINA for treatment of superficial papillary carcinoma of the urinary bladder is 60 mg in 30 mL to 60 mL of 0.9% Sodium Chloride Injection into the bladder by catheter. The solution should be retained for 2 hours. If the patient finds it impossible to retain 60 mL for 2 hours, the dose may be given in a volume of 30 mL. The patient may be repositioned every 15 minutes for maximum area contact. The usual course of treatment is once a week for 4 weeks. The course may be repeated if necessary, but second and third courses must be given with caution since bone-marrow depression may be increased.

2.2 Preparation Instructions

TEPADINA is a hazardous drug. Follow applicable special handling and disposal procedures. ^1

Use appropriate aseptic technique.

Preparation from the Vial

Reconstitution of the vial

- Reconstitute each TEPADINA vial with Sterile Water for Injection using the volumes described in Table 2.

Table 2: Reconstitution Volumes for the Vials

Strength | Amount of Sterile Water for Injection required for reconstitution | Final concentration
15 mg vial | 1.5 mL | 10 mg/mL
100 mg vial | 10 mL | 10 mg/mL

- Mix the vial by repeated inversions until the powder is completely dissolved. Visually inspect reconstituted solution in the vial for particulate matter and discoloration. The reconstituted solution may occasionally show opalescence.

- Use the reconstituted solution immediately. If not used immediately, store the reconstituted solution in the vial refrigerated at 2°C to 8°C (36°F to 46°F), for up to 80 hours.

- Dilution of the reconstituted vial into an infusion bag
  - Withdraw the required volume of the reconstituted solution from the TEPADINA vial. Discard any unused portion.
  - Transfer the reconstituted solution into an intravenous bag containing 0.9% Sodium Chloride Injection to obtain a final concentration between 0.5 mg/mL and 1 mg/mL. Gently mix the intravenous bag by slowly inverting the bag.
  - Use the diluted solution immediately. If the diluted solution is not used immediately, store refrigerated at 2°C to 8°C (36°F to 46°F) for up to 48 hours or room temperature at 25°C (77°F) for up to 6 hours.
- Administration
  - Parenteral drug products should be inspected visually for particulate matter and discoloration prior to administration, whenever solution and container permit. Use TEPADINA diluted solutions only if free of visible particulate matter.
  - For intravenous administration of high doses in the preparative regimen for allogeneic HSCT for beta thalassemia, administer by intravenous infusion via central venous catheter over 3 hours using an infusion set equipped with 0.2 micron filter.
  - For intravesicular administration into the bladder by catheter, see further instructions in Dosage and Administration Section 2.1.
  - For all other indications, see further instructions in Dosage and Administration Section 2.1.
  Preparation from the Multichamber Flexible Bag
  See the Instructions for Use in Subsection 2.3 for illustrated steps for preparation and administration of TEPADINA from the multichamber flexible bag.
- Activation of the TEPADINA Multichamber Flexible Bag
  - Activate the multichamber flexible bag by pressing firmly and applying uniform pressure with the palms of your overlapped hands until the peel seal is broken.
  - Mix gently until the reconstituted solution is completely dissolved.
  - Administer TEPADINA immediately after reconstitution of the multichamber flexible bag. If not used immediately, store refrigerated at 2°C to 8°C (36°F to 46°F) for up to 168 hours or at room temperature at 20°C to 25°C (68°F to 77°F) up to 56 hours.
- Administration

- Parenteral drug products should be inspected visually for particulate matter and discoloration prior to administration, whenever solution and container permit. Solution should be colorless and without particulate matter.
- After activation, the resultant concentration is 1 mg/mL.
- 200 mg or 400 mg dose can be directly administered from the multichamber flexible bag after activation.
- For doses other than 200 mg or 400 mg, withdraw the patient-specific dose from the multichamber flexible bag for transfer to a separate empty bag for administration. No further dilution is necessary.
- Administer using a 0.2 micron filter.

2.3 Instructions for Use of the Multichamber Flexible Bag:

Multichamber Flexible Bag Use Instructions
Figure A; 1 - Overwrap Notch |  | Figure B; 2 – NEVER use this port; 3 – Luer Port; 4 – Twist off Port; 5 – Label Area; 6 – Peel Seal (Must break to activate); 7 – Hole (For hanging the bag); 8 – Diluent chamber; 9 – Lyophilized powder chamber; TEPADINA® 200 mg; TEPADINA® 400 mg
1 – REMOVE OVERWRAP
a) Place bag on a clean, stable surface before opening.; b) Tear from overwrap notch, located close to the ports (Figure A – point 1).; c) Tear short sides open to access the inner bag as per Figure C. Figure C | d) Remove the multichamber flexible bag from the aluminum overwrap and unfold the bag Figure D.; Figure D
2 - INSPECT BAG PRIOR TO ACTIVATION | 3 – ACTIVATE THE BAG
Place bag on a clean, stable surface with the ports pointing away from you, as per Figure E.; Check that there are no liquid or product leakages from the connection ports 2, 3, 4 and from the chambers 8, 9.; Check the integrity of peel seal 6, verifying the absence of liquid in the chamber 9.; Figure E; TEPADINA 200 mg®; TEPADINA® 400 mg |  | Overlap your hands, on the lower portion of chamber 8 (as per Figure F).; Press firmly and apply uniform pressure until peel seal 6 is completely activated (it may take up to 5 seconds of continued pressure to break the peel seal 6).; Figure F; TEPADINA 200 mg®; TEPADINA® 400 mg
BAG BEFORE ACTIVATION | BAG AFTER ACTIVATION
Figure G |  | Figure H
Do NOT squeeze. |  | Figure I
4 – INSPECT BAG TO CONFIRM ACTIVATION
Check the peel seal 6 is now completely activated.; Chamber 8 and 9 are merged.; If the bag is not activated, refer to Step 3.; Figure J | Mix gently until complete dissolution of product.; After activation, the resultant concentration is 1 mg/mL.; A dose of 200 mg or 400 mg may be directly infused from the bag (see Step 6). For doses less than 200 mg or 400 mg see Step 5.; Figure K
5 – DOSE PREPARATION – for doses less than 200 mg or 400 mg withdraw the patient-specific dose from the TEPADINA® multichamber flexible bag and transfer to an appropriately-sized, empty, sterile bag for intravenous infusion.
Identify the Luer Port 3 if withdrawing a dose is needed.; Remove the plastic cap from Luer Port.; Figure L | Screw the luer lock device as per Figure M.; Do not use unproper non luer lock devices on port 3.; Figure M; Ensure that the connection is fully seated and tighten. | Withdraw the desired dose from TEPADINA® bag. This may require multiple graduated syringes depending on the desired dose. Unscrew each syringe counter-clockwise when finished.; Figure N; Replace the plastic cap on the Luer-Lock port 3.; Attach a needle or an appropriate closed-system transfer device to each syringe containing thiotepa solution and transfer the contents to an appropriately-sized, empty, sterile bag for intravenous infusion.; Discard the unused portion of the TEPADINA® bag. Follow applicable special handling and disposal procedures.
6 – CONNECTION for administration of 200 mg or 400 mg - The infusion set may be connected to the bag through either the spike connector OR the luer connector.
OPTION A – SPIKE CONNECTION; Identify Twist off port 4.; Twist off the plastic cap before inserting the spike.; Figure O; Insert the spike connector.; Figure P |  | OPTION B– LUER CONNECTION; Select luer cap port 3.; Remove the plastic cap from luer port 3 before connecting the luer connector.; Figure Q; Insert the luer connector.; Figure R; Ensure that the connection is fully seated and tighten.
7 – HANG THE BAG
Hang the bag by the hole 7. |  | Figure S

3 DOSAGE FORMS AND STRENGTHS

- For injection:15 mg, lyophilized white powder in single-dose vial for reconstitution.

- For injection:100 mg, lyophilized white powder in single-dose vial for reconstitution.
- For injection: 200 mg, lyophilized white powder thiotepa and 200 mL 0.9% Sodium Chloride Injection in single-dose multichamber flexible bag for reconstitution.
- For injection: 400 mg, lyophilized white powder thiotepa and 400 mL 0.9% Sodium Chloride Injection in single-dose multichamber flexible bag for reconstitution.

4 CONTRAINDICATIONS

TEPADINA is contraindicated in:

- Patients with severe hypersensitivity to thiotepa [see Warnings and Precautions (5.2)]
- Concomitant use with live or attenuated vaccines [see Warnings and Precautions (5.4)]

5 WARNINGS AND PRECAUTIONS

5.1 Myelosuppression

The consequence of treatment with high doses of TEPADINA together with other chemotherapy at the recommended dose and schedule in the preparative regimen for class 3 beta- thalassemia is profound myelosuppression occurring in all patients. Do not begin the preparative regimen if a stem cell donor is not available. Monitor complete blood counts, and provide supportive care for infections, anemia and thrombocytopenia until there is adequate hematopoietic recovery.

For patients receiving TEPADINA for treatment of adenocarcinoma of the breast, adenocarcinoma of the ovary, malignant effusions and superficial papillary carcinoma of the urinary bladder, if the bone marrow has been compromised by prior irradiation or chemotherapy, or is recovering from chemotherapy, the risk of severe myelosuppression with TEPADINA may be increased. Perform periodic complete blood counts during the course of treatment with TEPADINA. Provide supportive care for infections, bleeding, and symptomatic anemia [see Adverse Reactions (6.1)].

5.2 Hypersensitivity

Clinically significant hypersensitivity reactions, including anaphylaxis, have occurred following administration of TEPADINA. If anaphylactic or other clinically significant allergic reaction occurs, discontinue treatment with TEPADINA, initiate appropriate therapy, and monitor until signs and symptoms resolve [see Contraindications (4), Adverse Reactions (6.1)].

5.3 Cutaneous Toxicity

TEPADINA and/or its active metabolites may be excreted in part via skin patients receiving high-dose therapy. Treatment with TEPADINA may cause skin discoloration, pruritus, blistering, desquamation, and peeling that may be more severe in the groin, axillae, skin folds, in the neck area, and under dressings. Instruct patients to shower or bathe with water at least twice daily through 48 hours after administration of TEPADINA. Change occlusive dressing and clean the covered skin at least twice daily through 48 hours after administration of TEPADINA. Change bed sheets daily during treatment.

Skin reactions associated with accidental exposure to TEPADINA may also occur. Wash the skin thoroughly with soap and water in case TEPADINA solution contacts the skin. Flush mucous membranes in case of TEPADINA contact with mucous membranes.

5.4 Concomitant Use of Live and Attenuated Vaccines

Do not administer live or attenuated viral or bacterial vaccines to a patient treated with TEPADINA until the immunosuppressive effects have resolved.

5.5 Hepatic Veno-Occlusive Disease

Hepatic veno-occlusive disease may occur in patients who have received high-dose TEPADINA in conjunction with busulfan and cyclophosphamide [see Adverse Reactions (6.1)]. Monitor by physical examination, serum transaminases and bilirubin daily through BMT Day +28, and provide supportive care to patients who develop hepatic veno-occlusive disease.

5.6 Central Nervous System Toxicity

Fatal encephalopathy has occurred in patients treated with high doses of thiotepa. Other central nervous system toxicities, such as headache, apathy, psychomotor retardation, disorientation, confusion, amnesia, hallucinations, drowsiness, somnolence, seizures, coma, inappropriate behaviour and forgetfulness have been reported to occur in a dose-dependent manner during or shortly after administration of high-dose thiotepa. In pediatric patients treated with TEPADINA at the recommended dose in combination with busulfan and cyclophosphamide, 8% developed central nervous system toxicity (seizures and intracranial hemorrhage). Do not exceed the recommended dose of TEPADINA. If severe or life-threatening central nervous system toxicity occurs, discontinue administration of TEPADINA and provide supportive care.

5.7 Carcinogenicity

Like many alkylating agents, thiotepa has been reported to be carcinogenic when administered to laboratory animals [see Nonclinical Toxicity (13.1)]. Carcinogenicity is shown most clearly in studies using mice, but there is some evidence of carcinogenicity in man. There is an increased risk of a secondary malignancy with use of TEPADINA.

5.8 Embryo-Fetal Toxicity

Based on the mechanism of action and findings in animals, TEPADINA can cause fetal harm when administered to a pregnant woman. There are no adequate and well-controlled studies of TEPADINA in pregnant women. Thiotepa given by the intraperitoneal (IP) route was teratogenic in mice at doses ≥ 1 mg/kg (3.2 mg/m^2), approximately 8-fold less than the maximum recommended human therapeutic dose (0.8 mg/kg, 27 mg/m^2), based on body-surface area. Thiotepa given by the IP route was teratogenic in rats at doses ≥ 3 mg/kg (21 mg/m^2), approximately equal to the maximum recommended human therapeutic dose, based on body-surface area. Thiotepa was lethal to rabbit fetuses at a dose of 3 mg/kg (41 mg/m^2), approximately two times the maximum recommended human therapeutic dose based on body-surface area.

Advise pregnant women of the potential risk to the fetus [see Use in Specific Populations (8.1, 8.3)]. Advise females of reproductive potential to use highly effective contraception during and after treatment with TEPADINA for 6 months after therapy. Advise males of reproductive potential to use effective contraception during and after treatment with TEPADINA for 1 year after therapy [see Use in Specific Populations (8.1, 8.3)].

6 ADVERSE REACTIONS

The following clinically significant adverse reactions are described elsewhere in the labeling:

- Myelosuppression [see Warnings and Precautions (5.1)]
- Infection [see Warnings and Precautions (5.1)]
- Hypersensitivity [see Warnings and Precautions (5.2)]
- Cutaneous Toxicity [see Warnings and Precautions (5.3)]
- Hepatic Veno-Occlusive Disease [see Warnings and Precautions (5.5)]
- Central Nervous System Toxicity [see Warnings and Precautions (5.6)]
- Carcinogenicity [see Warnings and Precautions (5.7)]

6.1 Clinical Trials Experience

Because clinical trials are conducted under widely varying conditions, adverse reaction rates observed in the clinical trials of a drug cannot be directly compared to rates in the clinical trials of another drug and may not reflect the rates observed in practice.

Adverse Reactions With the Preparative Regimen for Class 3 Beta-Thalassemia

The safety of TEPADINA was evaluated by retrospective analysis of 76 pediatric patients with class 3 beta-thalassemia who underwent allogeneic hematopoietic progenitor (stem) cell transplantation (HSCT) using busulfan and cyclophosphamide with TEPADINA (n=25) or without TEPADINA (n=51) [see Clinical Studies (14)]. Adverse reactions were abstracted retrospectively from the medical records.

Serious adverse events that occurred in the TEPADINA-treated and control cohort were, respectively: gastrointestinal hemorrhage (4% vs 2%), pneumonia (4% vs 0), seizure (4% vs 2%), subarachnoid hemorrhage (4% vs 0) and veno-occlusive disease (4% vs 2%). By 90 days after HSCT, grades 2 to 4 acute graft-versus-host disease was observed in 7 (28%) patients in the TEPADINA cohort and in 13 (26%) patients in the control cohort. By 1-year after transplantation, chronic graft-versus-host disease was observed in 8 (35%) of 23 evaluable patients in the TEPADINA cohort, and 7 (14%) of 49 evaluable patients in the control cohort.

Adverse reactions occurring in at least 5% of patients treated with TEPADINA from start of the preparative regimen through 30 days after transplantation are shown in Table 3.

Table 3: Common Adverse Reactions (>5%) Occurring Through 30 Days After Transplantation In Patients With Class 3 Beta-Thalassemia Using Busulfan And Cyclophosphamide With Or Without TEPADINA in the Preparative Regimen

 | Preparative Regimen of Busulfan and Cyclophosphamide
 | With TEPADINA; N=25 patients (%) |  | Without TEPADINA; N=51 patients (%)
Adverse Reaction | Any Grade | Grade 3-5^1 | Any Grade | Grade 3-5^1
Mucositis^2 | 16 (64%) | 4 (16%) | 22 (43%) | 1 (2%)
Cytomegalovirus Infection | 12 (48%) | 0 | 15 (29%) | 0
Hemorrhage^3 | 7 (28%) | 2 (8%) | 12 (24%) | 3 (6%)
Diarrhea | 6 (24%) | 0 | 7 (14%) | 2 (4%)
Hematuria^4 | 5 (20%) | 0 | 10 (20%) | 3 (6%)
Rash^5 | 3 (12%) | 0 | 11 (22%) | 0
Intracranial Hemorrhage^6 | 2 (8%) | 1 (4%) | 0 | 0
Pseudomonas Infection | 2 (8%) | 0 | 0 | 0

^1Severe, life-threatening or fatal

^2Mucositis includes mouth hemorrhage, mucosal inflammation and stomatitis

^3Hemorrhage includes all hemorrhage terms

^4Hematuria includes cystitis hemorrhagic and hematuria

^5Rash includes dermatitis exfoliative, palmar erythema, rash, rash maculo-papular, rash pruritic and skin toxicity

^6Hemorrhage Intracranial includes hemorrhage intracranial and subarachnoid hemorrhage

All patients in the TEPADINA-treated and control cohorts developed profound cytopenias, including neutropenia, anemia, thrombocytopenia. Table 4 shows the selected chemistry abnormalities that occurred from start of the preparative regimen through 30 days after transplantation.

Table 4: Selected Laboratory Abnormalities Occurring Through 30 Days After Transplantation In Patients With Class 3 Beta-Thalassemia Using Busulfan And Cyclophosphamide With Or Without TEPADINA in the Preparative Regimen

 | Preparative Regimen of Busulfan and Cyclophosphamide
 | With TEPADINA; N=25 patients (%) |  | Without TEPADINA; N=51 patients (%)
Adverse Reaction | Any Grade | Grade 3-4 | Any Grade | Grade 3-4
Elevated alanine aminotransferase | 22 (88%) | 6 (24%) | 49 (96%) | 14 (27%)
Elevated aspartate aminotransferase | 20 (80%) | 4 (16%) | 45 (88%) | 9 (18%)
Elevated total bilirubin | 20 (80%) | 4 (16%) | 39 (77%) | 2 (4%)

Adverse Reactions with Treatment of adenocarcinoma of the breast, adenocarcinoma of the ovary, malignant effusions and superficial papillary carcinoma of the urinary bladder

Gastrointestinal: Nausea, vomiting, abdominal pain, anorexia.

General: Fatigue, weakness. Febrile reaction and discharge from a subcutaneous lesion may occur as the result of breakdown of tumor tissue.

Hypersensitivity Reactions: Allergic reactions - rash, urticaria, laryngeal edema, asthma, anaphylactic shock, wheezing.

Local Reactions: Contact dermatitis, pain at the injection site.

Neurologic: Dizziness, headache, blurred vision.

Renal: Dysuria, urinary retention, chemical cystitis or hemorrhagic cystitis.

Reproductive: Amenorrhea, interference with spermatogenesis.

Respiratory: Prolonged apnea has been reported when succinylcholine was administered prior to surgery, following combined use of thiotepa and other anticancer agents. It was theorized that this was caused by decrease of pseudocholinesterase activity caused by the anticancer drugs.

Skin: Dermatitis, alopecia. Skin depigmentation has been reported following topical use.

Special Senses: Conjunctivitis.

6.2 Postmarketing Experience

The following adverse reactions have been identified during post approval use of TEPADINA in preparative regimens prior to allogeneic or autologous hematopoietic progenitor (stem) cell transplantation (HSCT) in adult and pediatric patients. Because these reactions are reported voluntarily from a population of uncertain size, it is not always possible to reliably estimate their frequency or establish a causal relationship to drug exposure.

Blood and lymphatic system disorders: Febrile bone marrow aplasia.

Cardiac disorders: Bradycardia, cardiac failure congestive, cardio-respiratory arrest, pericardial effusion, pericarditis, right ventricular hypertrophy.

Congenital, familial and genetic disorders: Aplasia.

Ear and labyrinth disorders: Deafness.

Eye disorders: Blindness, eyelid ptosis, papilledema, strabismus.

Gastrointestinal disorders: Ascites, dysphagia, enterocolitis, gastritis, palatal disorder.

General disorders and administration site conditions: Device related infection, gait disturbance, malaise, multi-organ failure, pain.

Hepatobiliary disorders: Hepatomegaly.

Immune system disorders: Bone marrow transplant rejection, immunosuppression.

Infections and infestations: Acute sinusitis, bronchopulmonary aspergillosis, candida sepsis, enterococcal infection, Epstein-Barr virus infection, Escherichia sepsis, Fusarium infection, gastroenteritis, infection, lower respiratory tract infection fungal, lower respiratory tract infection viral, parainfluenza virus infection, Pneumonia legionella, relapsing fever, respiratory tract infection, sepsis, septic shock, Staphylococcal bacteremia, Staphylococcal infection, systemic candida, urinary tract infection.

Injury, poisoning and procedural complications: Refractoriness to platelet transfusion, subdural hematoma.

Investigations: Coagulation test abnormal, hemoglobin decreased, Klebsiella test positive, nuclear magnetic resonance imaging brain abnormal, transaminases increased, weight increased.

Metabolism and nutrition disorders: Hyponatremia.

Neoplasms benign, malignant and unspecified (incl. cysts and polyps): Breast cancer metastatic, central nervous system lymphoma, leukemia recurrent, lymphoma, malignant neoplasm progression, metastatic neoplasm, post transplant lymphoproliferative disorder.

Nervous system disorders: Aphasia, brain injury, bulbar palsy, central nervous system lesion, cerebral microangiopathy, cerebral ventricle dilatation, cerebrovascular accident, cognitive disorder, convulsion, coordination abnormal, encephalitis, encephalopathy, hemiplegia, hypotonia, leukoencephalopathy, memory impairment, motor dysfunction, neurotoxicity, quadriparesis, speech disorder, tremor, VIIth nerve paralysis, white matter lesion.

Psychiatric disorders: Delirium, depression, disorientation, suicidal ideation.

Renal and urinary disorders: Renal failure, nephropathy toxic.

Respiratory, thoracic and mediastinal disorders: Acute respiratory distress, aspiration, dyspnea exertional, interstitial lung disease, lung disorder, pneumonitis, pulmonary arteriopathy, pulmonary sepsis, pulmonary veno-occlusive disease, respiratory distress, respiratory failure, pulmonary hypertension.

Skin and subcutaneous tissue disorders: Stevens-Johnson syndrome and toxic epidermal necrolysis.

Vascular disorders: Capillary leak syndrome.

7 DRUG INTERACTIONS

7.1 Effect of Cytochrome CYP3A Inhibitors and Inducers

In vitro studies suggest that thiotepa is metabolized by CYP3A4 and CYP2B6 to its active metabolite TEPA. Avoid co-administration of strong CYP3A4 inhibitors (e.g., itraconazole, clarithromycin, ritonavir) and strong CYP3A4 inducers (e.g., rifampin, phenytoin) with TEPADINA due to the potential effects on efficacy and toxicity [see Clinical Pharmacology (12.3)]. Consider alternative medications with no or minimal potential to inhibit or induce CYP3A4. If concomitant use of strong CYP3A4 modulators cannot be avoided, closely monitor for adverse drug reactions.

7.2 Effect of TEPADINA on Cytochrome CYP2B6 Substrates

In vitro studies suggest that thiotepa inhibits CYP2B6. TEPADINA may increase the exposure of drugs that are substrates of CYP2B6 in patients; however, the clinical relevance of this in vitro interaction is unknown [see Clinical Pharmacology (12.3)].

The administration of thiotepa with cyclophosphamide in patients reduces the conversion of cyclophosphamide to the active metabolite, 4-hydroxycyclophosphamide; the effect appears sequence dependent with a greater reduction in the conversion to 4-hydroxycyclophosphamide when thiotepa is administered 1.5 hours prior to the intravenous administration of cyclophosphamide compared to administration of thiotepa after intravenous cyclophosphamide [see Clinical Pharmacology (12.3)]. The reduction in 4-hydroxycyclophosphamide levels may potentially reduce efficacy of cyclophosphamide treatment.

8 USE IN SPECIFIC POPULATIONS

8.1 Pregnancy

Risk Summary

TEPADINA can cause fetal harm when administered to a pregnant woman based on findings from animals and the drug’s mechanism of action [see Clinical Pharmacology (12.1)]. Limited available data with TEPADINA use in pregnant women are insufficient to inform a drug-associated risk of major birth defects and miscarriage. In animal reproduction studies, administration of thiotepa to pregnant mice and rats during organogenesis produced teratogenic effects (neural tube defects and malformations of the skeletal system of the fetus) at doses approximately 0.125 and 1 times, respectively, the maximum recommended human daily dose on a mg/m^2 basis. Thiotepa was lethal to rabbit fetuses at approximately 2 times the maximum recommended human therapeutic dose based on body-surface area [see Data]. Consider the benefits and risks of TEPADINA for the mother and possible risks to the fetus when prescribing TEPADINA to a pregnant woman.

The estimated background risk of major birth defects and miscarriage for the indicated population is unknown. In the U.S. general population, the estimated background risk of major birth defects and miscarriage in clinically recognized pregnancies is 2-4% and 15-20%, respectively.

Data

Animal Data

Thiotepa given by the IP route in mice at doses ≥ 1 mg/kg (3.2 mg/m^2), approximately 8-fold less than the maximum recommended human therapeutic dose based on body-surface area, and in rats at doses ≥ 3 mg/kg (21 mg/m^2), approximately equal to the maximum recommended human therapeutic dose based on body-surface area, resulted in various malformations including neural tube defects, omphalocele, renal agenesis, atresia ani, limb and digit defects, cleft palate, micrognathia, other skeletal anomalies in the skull, vertebrae and ribs, and reduced skeletal ossification. Thiotepa was lethal to rabbit fetuses at a dose of 3 mg/kg (41 mg/m^2), approximately 2 times the maximum recommended human therapeutic dose based on body-surface area.

8.2 Lactation

Risk Summary

There is no information regarding the presence of thiotepa in human milk, the effects on the breastfed infant, or the effects on milk production.

Because of the potential for serious adverse reactions, including the potential for tumorigenicity shown for thiotepa in animal studies, advise patients not to breastfeed during TEPADINA treatment.

8.3 Females and Males of Reproductive Potential

TEPADINA can cause fetal harm when administered to a pregnant woman [see Use in Specific Populations (8.1)].

Pregnancy testing

Verify the pregnancy status of females of reproductive potential prior to initiating TEPADINA therapy.

Contraception

Females

Advise females of reproductive potential to avoid pregnancy during TEPADINA treatment and for 6 months after the final dose of TEPADINA. Advise females to immediately report pregnancy [see Use in Specific Populations (8.1)].

Males

TEPADINA may damage spermatozoa and testicular tissue, resulting in possible genetic abnormalities. Males with female sexual partners of reproductive potential should use effective contraception during TEPADINA treatment and for 1 year after the final dose of TEPADINA [see Nonclinical Toxicology (13.1)].

Infertility

Based on nonclinical findings, male and female fertility may be compromised by treatment with TEPADINA. Inform male patients about the possibility of sperm conservation before the start of therapy [see Nonclinical Toxicology (13.1)].

8.4 Pediatric Use

The safety and effectiveness of TEPADINA for prevention of graft rejection in pediatric patients undergoing allogeneic HSCT for class 3 beta-thalassemia was established in one prospective study and one retrospective study [see Clinical Studies (14)] that included 1 infant (1 month to 1 year), 23 children (2 to 11 years) and 13 adolescents (12 to 16 years) who received TEPADINA as part of their preparative regimen. Safety and effectiveness of TEPADINA in neonates have not been established.

Safety and effectiveness of TEPADINA for treatment of adenocarcinoma of the breast, adenocarcinoma of the ovary, malignant effusions and superficial papillary carcinoma of the urinary bladder in pediatric patients have not been established.

8.5 Geriatric Use

The safety and effectiveness of TEPADINA as a preparative regimen prior to allogeneic hematopoietic progenitor (stem) cell transplantation (HSCT) for patients with class 3 beta-thalassemia have not been established in geriatric patients. Clinical studies of TEPADINA for this indication did not include subjects aged 65 and over.

Clinical studies of TEPADINA for treatment of adenocarcinoma of the breast, adenocarcinoma of the ovary, malignant effusions and superficial papillary carcinoma of the urinary bladder did not include sufficient numbers of subjects aged 65 and over to determine whether elderly subjects respond differently from younger subjects, and other reported clinical experience has not identified differences in responses between the elderly and younger patients. In general, dose selection for an elderly patient should be cautious, usually starting at the low end of the dosing range, reflecting the greater frequency of decreasing hepatic, renal or cardiac function, and of concomitant disease or other drug therapy.

8.6 Renal Impairment

In patients with moderate (creatinine clearance (CLcr) of 30 mL/min to 59 mL/min) renal impairment, decreased renal excretion may result in increased plasma levels of thiotepa and TEPA [see Clinical Pharmacology (12.3)]. This may result in increased toxicity. Monitor patients with moderate to severe (CLcr < 30 mL/min) renal impairment for signs and symptoms of toxicity following treatment with TEPADINA for an extended period of time.

8.7 Hepatic Impairment

Thiotepa is extensively metabolized in the liver. Patients with moderate (bilirubin levels greater than 1.5 times to 3 times the upper limit of normal and any AST) hepatic impairment may have increased plasma levels of thiotepa [see Clinical Pharmacology (12.3)]. This may result in toxicity. Monitor patients with moderate to severe (bilirubin levels greater than 3 times upper limit of normal and any AST) hepatic impairment for signs and symptoms of toxicity following treatment with TEPADINA for an extended period of time.

10 OVERDOSE

There is no experience with overdoses of thiotepa. The most important adverse reactions expected in case of overdose are myeloablation and pancytopenia [see Nonclinical Toxicology (13)]. There is no known antidote for thiotepa. Monitor the hematological status closely and provide vigorous supportive measures as medically indicated.

11 DESCRIPTION

TEPADINA (thiotepa) is an alkylating agent. TEPADINA (thiotepa) for injection is supplied as a non-pyrogenic, sterile lyophilized white powder for intravenous, intracavitary, or intravesical use after reconstitution and dilution.

TEPADINA is available

- In a single-dose vial containing 15 mg thiotepa. After reconstitution with 1.5 mL of Sterile Water for Injection, each mL contains 10 mg thiotepa;
- In a single-dose vial containing 100 mg thiotepa. After reconstitution with 10 mL of Sterile Water for Injection, each mL contains 10 mg thiotepa;
- In a single-dose multichamber flexible bag containing 200 mg thiotepa and 200 mL 0.9% Sodium Chloride Injection;
- In a single-dose multichamber flexible bag containing 400 mg thiotepa and 400 mL 0.9% Sodium Chloride Injection;

Thiotepa is a synthetic product with antitumor activity. The chemical name for thiotepa is Tris(1-aziridinyl)phosphine sulfide. Thiotepa has the following structural formula:

Thiotepa has the molecular formula C6H12N3PS, and a molecular weight of 189.23, and it appears as fine, white crystalline flakes, with a melting range of 52°C to 57°C. It is soluble in water and organic solvents. When reconstituted with sterile water for injection, the resulting solution has a pH of approximately 5.5 to 7.5. Thiotepa is unstable in acid medium.

12 CLINICAL PHARMACOLOGY

12.1 Mechanism of Action

Thiotepa is a cytotoxic agent of the polyfunctional type, related chemically and pharmacologically to the nitrogen mustard. The radiomimetic action of thiotepa is believed to occur through the release of ethyleneimine radicals which, like irradiation, disrupt the bonds of DNA. One of the principle bond disruptions is initiated by alkylation of guanine at the N-7 position, which severs the linkage between the purine base and the sugar and liberates alkylated guanines.

12.2 Pharmacodynamics

The exposure-response relationship for efficacy and safety has not been characterized.

12.3 Pharmacokinetics

Absorption

Thiotepa reached maximal concentrations close to the end infusion following an intravenous infusion.

Distribution

The binding of thiotepa to plasma proteins is approximately 10% to 20%. The mean volume of distribution (% coefficient of variation) of thiotepa was 30 L/m^2 (44%) or 1.2 L/kg (47%) following a single intravenous infusion of TEPADINA at a dose of 5 mg/kg over 3 hours in pediatric population. In adults administered intravenous thiotepa between 20 mg to 250 mg/m^2 as an intravenous bolus or infusion up to 4 hours, the mean volume of distribution of thiotepa ranged from 1.0 L/kg (30%) to 1.9 L/kg (17%).

Elimination

Following a single intravenous infusion over 3 hours of TEPADINA at a dose of 5 mg/kg in pediatric population, the estimated mean (% coefficient of variation) clearance of thiotepa was 0.58 L/hr/kg (60%) or 13.8 L/hr/m^2 (52%). The mean terminal elimination half-life was 1.7 hours (64%) for thiotepa and 4 hours (29%) for its major active metabolite, N,N',N''-triethylenephosphoramide (TEPA) in pediatric population. In adults administered intravenous thiotepa between 20 mg to 250 mg/m^2 as an intravenous bolus or infusion up to 4 hours, the mean thiotepa clearance ranged from 14.6 L/hr/m^2 (23%) to 27.9 L/hr/m^2 (69%). In adult population, the mean terminal elimination half-life ranged from 1.4 hours (7%) to 3.7 hours (14%) for thiotepa and from 4.9 hours to 17.6 hours (20%) for TEPA.

Metabolism

Thiotepa undergoes hepatic metabolism. In vitro data suggests that CYP3A4 and CYP2B6 may be responsible for the metabolism of thiotepa to TEPA, a major active metabolite.

Excretion

In adult and pediatric patients, urinary excretion of thiotepa accounted for less than 2% of the dose and TEPA accounted for 11% or less of the dose.

Specific Populations

Hepatic Impairment

The clearance of thiotepa following a single TEPADINA dose of 5 mg/kg in pediatric population with mild hepatic impairment was similar to the clearance observed in patients with normal liver function administered thiotepa.

The exposure (as measured by area under the curve (AUC)) of thiotepa increased by 1.6-fold and 1.8-fold following administration of multiple thiotepa doses of 7 mg/kg administered every 2 days with cyclophosphamide in two adult patients who had liver metastases with moderate hepatic impairment compared to the exposure observed in one patient with normal hepatic function. The effect of severe hepatic impairment on thiotepa exposure is unknown.

Renal Impairment

The exposure (as measured by AUC) of thiotepa increased by 1.4-fold and TEPA increased by 2.6-fold following administration of multiple doses of 120 mg/m^2/day in one patient with moderate renal impairment (CLcr = 38 mL/min) administered cyclophosphamide plus thiotepa plus carboplatin, compared to exposure of thiotepa in patients with normal renal function.The effects of severe renal impairment or end-stage renal disease on thiotepa exposure are unknown.

Drug Interactions

The clinical relevance of in vitro inhibition of the cytochrome P450 enzymes described below is unknown, but it cannot be excluded that the systemic exposure of thiotepa or medicinal products that are substrates for these enzymes may be affected with concomitant administration with TEPADINA.

Effect of Cytochrome P450 Modulators on Thiotepa

In vitro data demonstrates that CYP3A4 and CYP2B6 inhibitors decrease the metabolism of thiotepa [see Drug Interactions (7.1)].

Effect of Thiotepa on Cytochrome P450 2B6

In vitro data demonstrates that thiotepa inhibits CYP2B6.

Effect of Thiotepa on Cyclophosphamide

The administration of thiotepa 1.5 hours prior to intravenous cyclophosphamide in patients administered cyclophosphamide plus thiotepa plus carboplatin decreased the AUC of 4-hydroxycyclophosphamide by 26% and maximal concentrations of 4-hydroxycyclophosphamide by 62%, compared to administration of cyclophosphamide prior to thiotepa.

13 NONCLINICAL TOXICOLOGY

13.1 Carcinogenesis, Mutagenesis, Impairment of Fertility

In mice, repeated intraperitoneal (IP) administration of thiotepa (1.15 or 2.3 mg/kg three times per week for 52 or 43 weeks, respectively) produced a significant increase in the combined incidence of squamous-cell carcinomas of the skin, preputial gland, and ear canal, and combined incidence of lymphoma and lymphocytic leukemia. In other studies in mice, repeated IP administration of thiotepa (4 or 8 mg/kg three times per week for 4 weeks followed by a 20 week observation period or 1.8 mg/kg three times per week for 4 weeks followed by a 35 week observation period) resulted in an increased incidence of lung tumors. In rats, repeated IP administration of thiotepa (0.7 or 1.4 mg/kg three times per week for 52 or 34 weeks, respectively) produced significant increases in the incidence of squamous-cell carcinomas of the skin or ear canal, combined hematopoietic neoplasms, and uterine adenocarcinomas. Thiotepa given intravenously (IV) to rats (1 mg/kg once per week for 52 weeks) produced an increased incidence of malignant tumors (abdominal cavity sarcoma, lymphosarcoma myelosis, seminoma, fibrosarcoma, salivary gland hemangioendothelioma, mammary sarcoma, pheochromocytoma) and benign tumors.

The lowest reported carcinogenic dose in mice (1.15 mg/kg, 3.68 mg/m^2) is approximately 7-fold less than the maximum recommended human therapeutic dose based on body-surface area. The lowest reported carcinogenic dose in rats (0.7 mg/kg, 4.9 mg/m^2) is approximately 6-fold less than the maximum recommended human therapeutic dose based on body-surface area.

Thiotepa was mutagenic in in vitro assays in Salmonella typhimurium, E coli, Chinese hamster lung and human lymphocytes. Chromosomal aberrations and sister chromatid exchanges were observed in vitro with thiotepa in bean root tips, human lymphocytes, Chinese hamster lung, and monkey lymphocytes.

Mutations were observed with oral thiotepa in mouse at doses > 2.5 mg/kg (8 mg/m^2). The mouse micronucleus test was positive with intraperitoneal administration of > 1 mg/kg (3.2 mg/m^2). Other positive in vivo chromosomal aberration or mutation assays included Drosophila melanogaster, Chinese hamster marrow, murine marrow, monkey lymphocyte, and murine germ cell.

Thiotepa impaired fertility in male mice at oral or intraperitoneal doses ≥ 0.7 mg/kg (2.24 mg/m^2), approximately 12-fold less than the maximum recommended human therapeutic dose based on body-surface area. Thiotepa (0.5 mg) inhibited implantation in female rats when instilled into the uterine cavity. Thiotepa interfered with spermatogenesis in mice at IP doses ≥ 0.5 mg/kg (1.6 mg/m^2), approximately 17-fold less than the maximum recommended human therapeutic dose based on body-surface area. Thiotepa interfered with spermatogenesis in hamsters at an IP dose of 1 mg/kg (4.1 mg/m^2), approximately 7-fold less than the maximum recommended human therapeutic dose based on body-surface area.

14 CLINICAL STUDIES

TEPADINA was evaluated in a retrospective study of pediatric patients with class 3 beta-thalassemia who underwent allogeneic hematopoietic progenitor (stem) cell transplantation (HSCT) from a human leukocyte antigen (HLA)-identical sibling donor. Twenty-five patients (10 male and 15 female) of median age 10 years (range, 5-16 years) were treated with intravenous busulfan at weight-based dosing from Day -10 to Day -7 pretransplant [see Table 1], intravenous TEPADINA 5 mg/kg twice on Day -6, intravenous cyclophosphamide 40 mg/kg/day on Day -5 to Day -2, and marrow infusion on Day 0. All patients had also received precytoreduction with hydroxyurea, azathioprine and fludarabine prior to start of the preparative regimen.

Efficacy was based on the incidence of graft rejection (primary or late rejection). The incidence of graft rejection in these 25 patients using TEPADINA was 0% (95% CI: [0, 0.12]). Of the 51 patients who received the same preparative regimen, historically, without TEPADINA, the incidence of graft rejection reported was 25.5% (95% CI: [0.13, 0.37]).

15 REFERENCES

1. OSHA Hazardous Drugs. OSHA, http://www.osha.gov/SLTC/hazardousdrugs/index.html.

16 HOW SUPPLIED/STORAGE AND HANDLING

How Supplied

TEPADINA (thiotepa) for injection is a lyophilized white powder supplied in a carton containing one single-dose Type I clear glass vial with a rubber stopper (not made with natural rubber latex) or in an aluminum overwrap containing one single-dose multichamber flexible bag as:

TEPADINA 15 mg

One vial contains 15 mg thiotepa (NDC 70121-1630-1).

TEPADINA 100 mg

One vial contains 100 mg thiotepa (NDC 70121-1631-1).

TEPADINA 200 mg

One multichamber flexible bag contains 200 mg thiotepa and 200 mL 0.9% Sodium Chloride Injection (NDC 70121-2749-1).

TEPADINA 400 mg

One multichamber flexible bag contains 400 mg thiotepa and 400 mL 0.9% Sodium Chloride Injection (NDC 70121-1687-1).

Storage and Handling

TEPADINA multichamber flexible bag and vials must be stored and transported refrigerated at 2°C to 8°C (36°F to 46°F). Do not freeze. Keep the bag in the aluminum overwrap in order to protect it from activation.

TEPADINA is a hazardous drug. Follow applicable special handling and disposal procedures.^1

17 PATIENT COUNSELING INFORMATION

Hypersensitivity

Counsel patients on the signs and symptoms of hypersensitivity and to seek immediate emergency assistance if they develop any of these signs and symptoms [see Warnings and Precautions (5.2)].

Myelosuppression

Inform patients of the possibility of developing low blood cell counts and the need for hematopoietic progenitor cell infusion. Instruct patients to immediately report to their healthcare provider if bleeding or fever occurs [see Warnings and Precautions (5.1)].

Females and Males of Reproductive Potential

TEPADINA can cause fetal harm. Advise females receiving TEPADINA to avoid pregnancy during TEPADINA treatment and for 6 months after the last dose of TEPADINA [see Warnings and Precautions (5.8)].

Advise males with female sexual partners of reproductive potential to use effective contraception during TEPADINA treatment and for 1 year after the last dose of TEPADINA [see Use in Specific Populations (8.3)].

Advise females to report pregnancy immediately [see Warnings and Precautions (5.8)].

Advise patients that TEPADINA can produce infertility. Inform male patients about the possibility of sperm conservation before the start of therapy [see Use in Specific Populations (8.3)].

Lactation

Advise patients to avoid breastfeeding while receiving TEPADINA [see Use in Specific Populations (8.2)].

Secondary malignancies

Inform patients that TEPADINA can increase the risk of secondary malignancy [see Warnings and Precautions (5.7)].

Distributed by:

Amneal Pharmaceuticals LLC

Bridgewater, NJ 08807

for

ADIENNE SA

Switzerland

U.S. Pat. No. 9,931,458